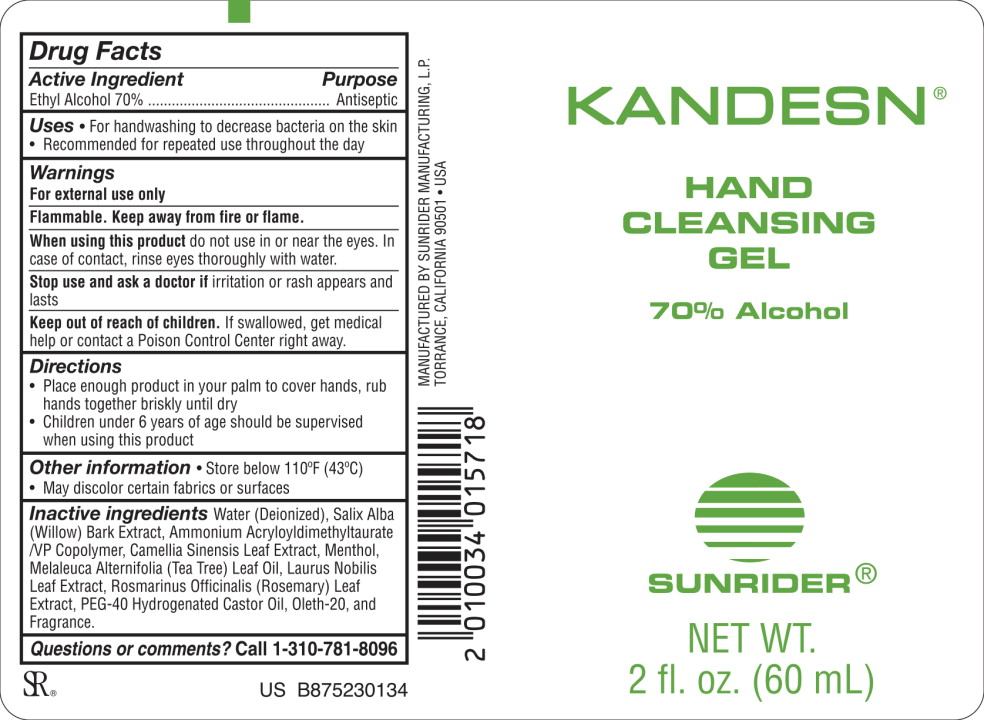 DRUG LABEL: Kandesn
NDC: 62191-085 | Form: GEL
Manufacturer: Sunrider Manufacturing L.P.
Category: otc | Type: HUMAN OTC DRUG LABEL
Date: 20200422

ACTIVE INGREDIENTS: Alcohol 70 mL/100 mL
INACTIVE INGREDIENTS: Water; Salix Alba Bark; Ammonium Acryloyldimethyltaurate/VP Copolymer; Green Tea leaf; Menthol, Unspecified Form; Tea Tree Oil; Bay Leaf; Rosemary; Polyoxyl 40 Hydrogenated Castor Oil; Oleth-20

Drug Facts

Active Ingredient

Ethyl Alcohol 70%

Purpose

Antiseptic

Uses

- For handwashing to decrease bacteria on the skin
- Recommended for repeated use throughout the day

Warnings

For external use only

Flammable. Keep away from fire or flame.

When using this product do not use in or near the eyes. Incase of contact, rinse eyes thoroughly with water.

Stop use and ask a doctor if irritation or rash appears and lasts

Keep out of reach of children. If swallowed, get medical help or contact a Poison Control Center right away.

Directions

- Place enough product in your palm to cover hands, rub hands together briskly until dry
- Children under 6 years of age should be supervised when using this product

Other information

Store below 110⁰F (43⁰C)

- May discolor certain fabrics or surfaces

Inactive ingredients

Water (Deionized), Salix Alba (Willow) Bark Extract, Ammonium Acryloyldimethyltaurate/VP Copolymer, Camellia Sinensis Leaf Extract, Menthol, Melaleuca Alternifolia (Tea Tree) Leaf Oil, Laurus Nobilis Leaf Extract, Rosmarinus Officinalis (Rosemary) Leaf Extract, PEG-40 Hydrogenated Castor Oil, Oleth-20, Fragrance

Questions or comments?

Call 1-310-781-8096

Principal Display Panel – 60 mL Bottle Label

KANDESN®

HAND
CLEANSING
GEL

70% Alcohol

SUNRIDER®

NET WT.

2 fl. oz. (60 mL)